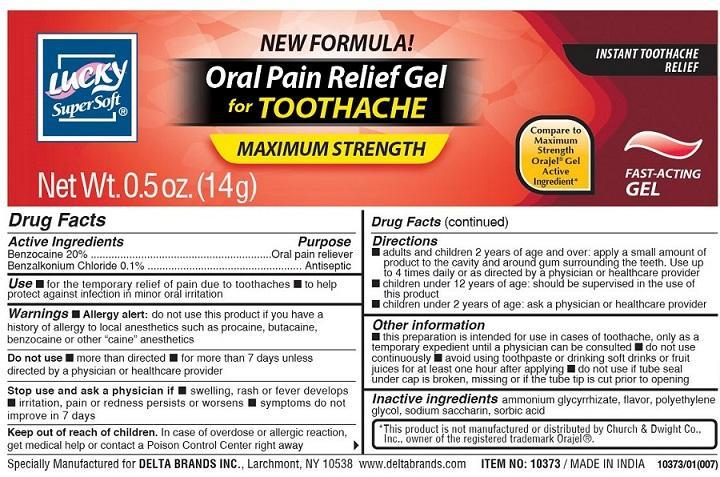 DRUG LABEL: Oral Gel
NDC: 83650-101 | Form: GEL
Manufacturer: Savvy Care and Cosmetics
Category: otc | Type: HUMAN OTC DRUG LABEL
Date: 20241219

ACTIVE INGREDIENTS: BENZOCAINE 20 g/100 g; BENZALKONIUM CHLORIDE 0.1 g/100 g
INACTIVE INGREDIENTS: AMMONIUM GLYCYRRHIZATE; POLYETHYLENE GLYCOL, UNSPECIFIED; SACCHARIN SODIUM; SORBIC ACID

Oral gel

Active Ingredient

Benzocaine 20%

Benzalkonium Chloride 0.1%

Purpose

Oral pain reliever

Antiseptic

Use

■ for the temporary relief of pain due to toothaches ■ to help protect against infectionin minor oral irritation

Warnings

■ Allergy alert:do not use this product if you have a history of allergy to local anesthetics such as procaine, butacaine or other "caine" anesthetics

Do not use

■ more than directed ■ for more than 7 days unless directed by a physician or healthcare provider

Stop use and ask a physician if

■ swelling, rash or fever develops ■ irritation, pain or redness persists or worsens ■ symptoms do not improve in 7 days

Keep out of reach of children

In case of overdose or allergic reaction get medical help or contact a Poison Control Center right away

Directions

■ adults and children 2 years of age and over: apply a small amount of the product to the cavity and around the gum surrounding the teeth Use up to 4 times daily or as directed by a physician or healthcare provider ■ children under 12 years: should be supervised in the use of this product ■ children under 2 years of age: ask a physician or health care provider

Other information

■ this preparation is intended for use in cases ot toothache, only as a temporary expedient until a physican can be consulted ■ do not use continuously ■ avoid using toothpaste or drinking soft drinks or fruit juices for at least one hour after applying ■ do not use if tube seal under cap is broken, missing or if the tube tip is cut prior to opening

Inactive ingredients

ammonium glycyrrhizate, flavor, polyethylene glycol, sodium saccharin, sorbic acid